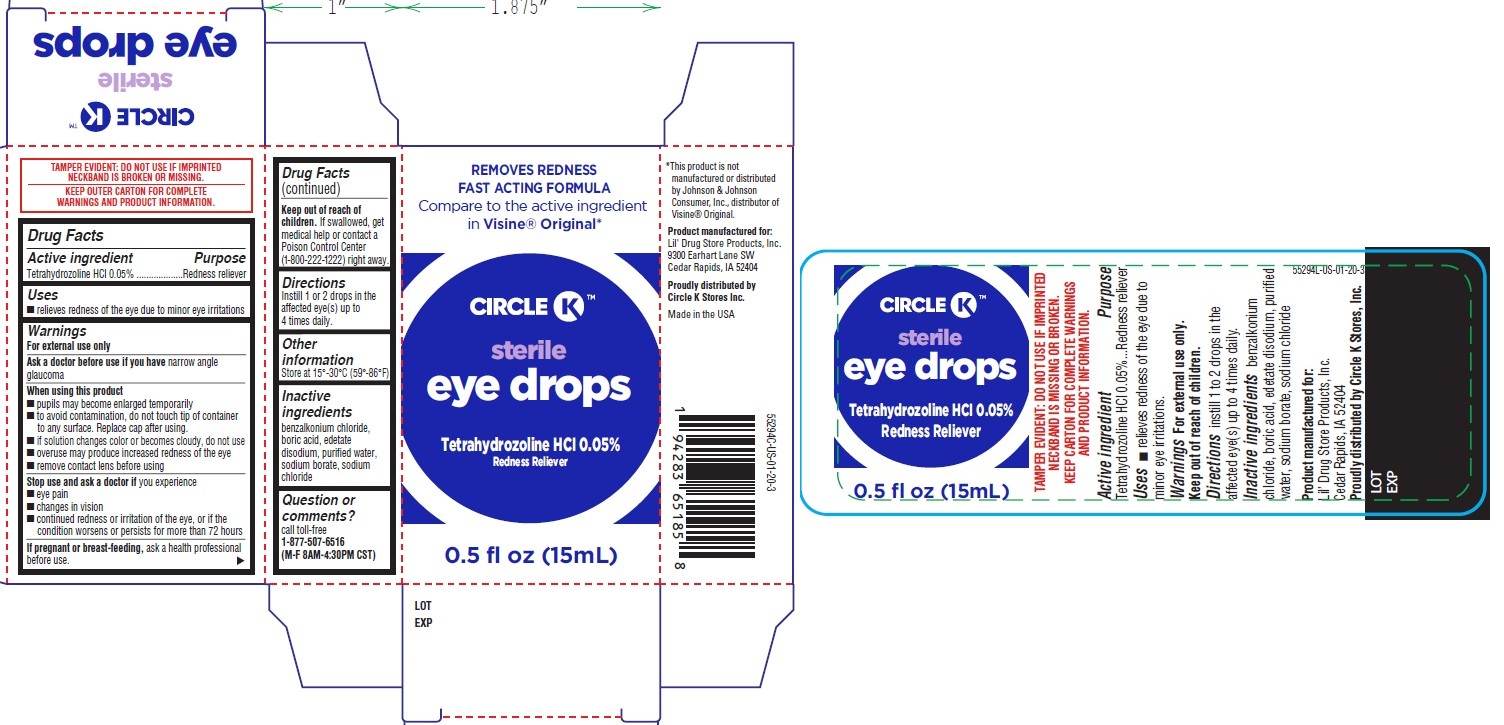 DRUG LABEL: Redness Reliever, Circle K
NDC: 66715-5429 | Form: LIQUID
Manufacturer: Lil' Drug Store products, Inc.
Category: otc | Type: HUMAN OTC DRUG LABEL
Date: 20251201

ACTIVE INGREDIENTS: TETRAHYDROZOLINE HYDROCHLORIDE 0.5 mg/1 mL
INACTIVE INGREDIENTS: BENZALKONIUM CHLORIDE; SODIUM BORATE; WATER; BORIC ACID; EDETATE DISODIUM; SODIUM CHLORIDE

Redness Reliever, Circle K™

Drug Facts

Active ingredient

Tetrahydrozoline HCl 0.05%

Purpose

Redness reliever

Uses

- relieves redness of the eye due to minor eye irritations

Warnings

For external use only

Ask a doctor before use if you have narrow angle glaucoma

When using this product

- pupils may become enlarged temporarily
- to avoid contamination, do not touch tip of container to any surface. Replace cap after using.
- if solution changes color or becomes cloudy, do not use
- overuse may produce increased redness of the eye
- remove contact lens before using

Stop use and ask a doctor if you experience

- eye pain
- changes in vision
- continued redness or irritation of the eye, or if the condition worsens or persists for more than 72 hours

If pregnant or breast-feeding, ask a health professional before use.

Keep out of reach of children. If swallowed, get medical help or contact a Poison Control Center (1-800-222-1222) right away.

Directions

Instill 1 or 2 drops in the affected eye(s) up to 4 times daily.

Other information

Store at 15°-30°C (59°-86°F)

Inactive ingredients

benzalkonium chloride, boric acid, edetate disodium, purified water, sodium borate, sodium chloride

Question or comments?

call toll-free 1-877-507-6516 (M-F 8AM-4:30PM CST)

Redness Reliever, Circle K™ PDP/Package

REMOVES REDNESS
FAST ACTING FORMULA

Compare to the active ingredient
in Visine® Original*

[Circle K logo]

sterile
eye drops

Tetrahydrozoline HCI 0.05%
Redness Reliever

0.5 fl oz (15mL)